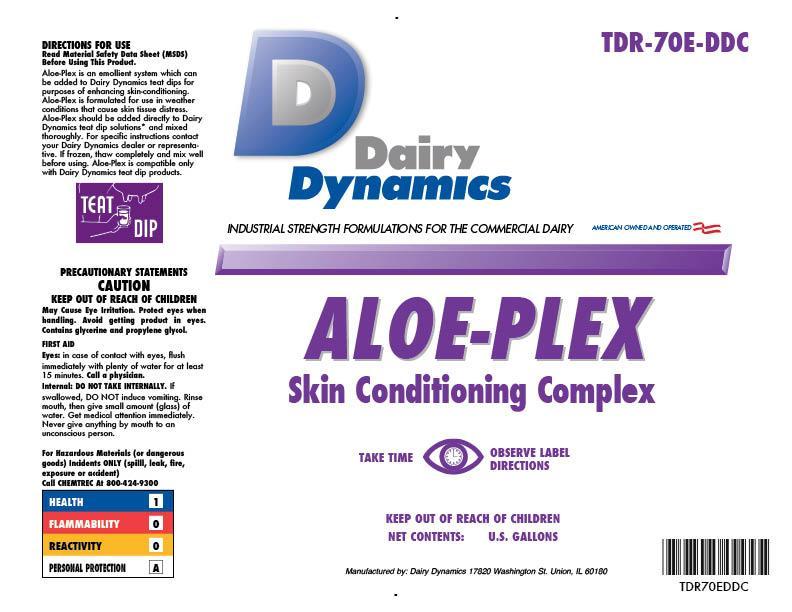 DRUG LABEL: ALOE-PLEX
NDC: 67351-970 | Form: SOLUTION
Manufacturer: Dairy Dynamics L.L.C.
Category: animal | Type: OTC ANIMAL DRUG LABEL
Date: 20150108

ACTIVE INGREDIENTS: ALOE VERA LEAF 0.012 g/1 L
INACTIVE INGREDIENTS: WATER; GLYCERIN; LANOLIN; PROPYLENE GLYCOL

ALOE-PLEX
Skin Conditioning Complex

DIRECTIONS FOR USE

Read Material Safety Data Sheet (MSDS) Before Using This Product.

Aloe-Plex is an emollient system which can be added to Dairy Dynamics teat dips for purpose of enhancing skin-conditioning. Aloe-Plex is formulated for use in weather conditions that cause skin tissue distress. Aloe-Plex should be added directly to Dairy Dynamics teat solutions* and mixed thoroughly. For specific instructions contact your Dairy Dynamics dealer or representative. If frozen, thaw completely and mix well before using. Aloe-Plex is compatible only with Dairy Dynamics teat dip products.

TEAT DIP

PRECAUTIONS

PRECAUTIONARY STATEMENTS

CAUTION

KEEP OUT OF REACH OF CHILDREN

May Cause Eye Irritation. Protect eyes when handling. Avoid getting product in eyes. Contains glycerine and propylene glycol.

FIRST AID

Eyes: in case of contact with eyes, flush immediately with plenty of water for at least 15 minutes. Call a physician.

Internal: DO NOT TAKE INTERNALLY. If swallowed, DO NOT induce vomiting. Rinse mouth, then give a small amount (glass) of water. Get medical attention immediately. Never give anything by mouth to an unconscious person.

WARNINGS

For Hazardous Materials (or dangerous goods) Incidents ONLY (spill, leak, fire, exposure, or accident)

Call CHEMTREC At 800-424-9300

HEALTH 1

FLAMMABILITY 0

REACTIVITY 0

PERSONAL PROTECTION A

ALOE-PLEX

Skin Conditioning Complex

PRECAUTIONS

TAKE TIME OBSERVE LABEL DIRECITONS

KEEP OUT OF REACH OF CHILDREN

NET CONTENTS: U.S. GALLONS

Manufactured by: Dairy Dynamics 17820 Washington St. Union, IL 60180

TDR-70E-DDC

TDR70EDDC